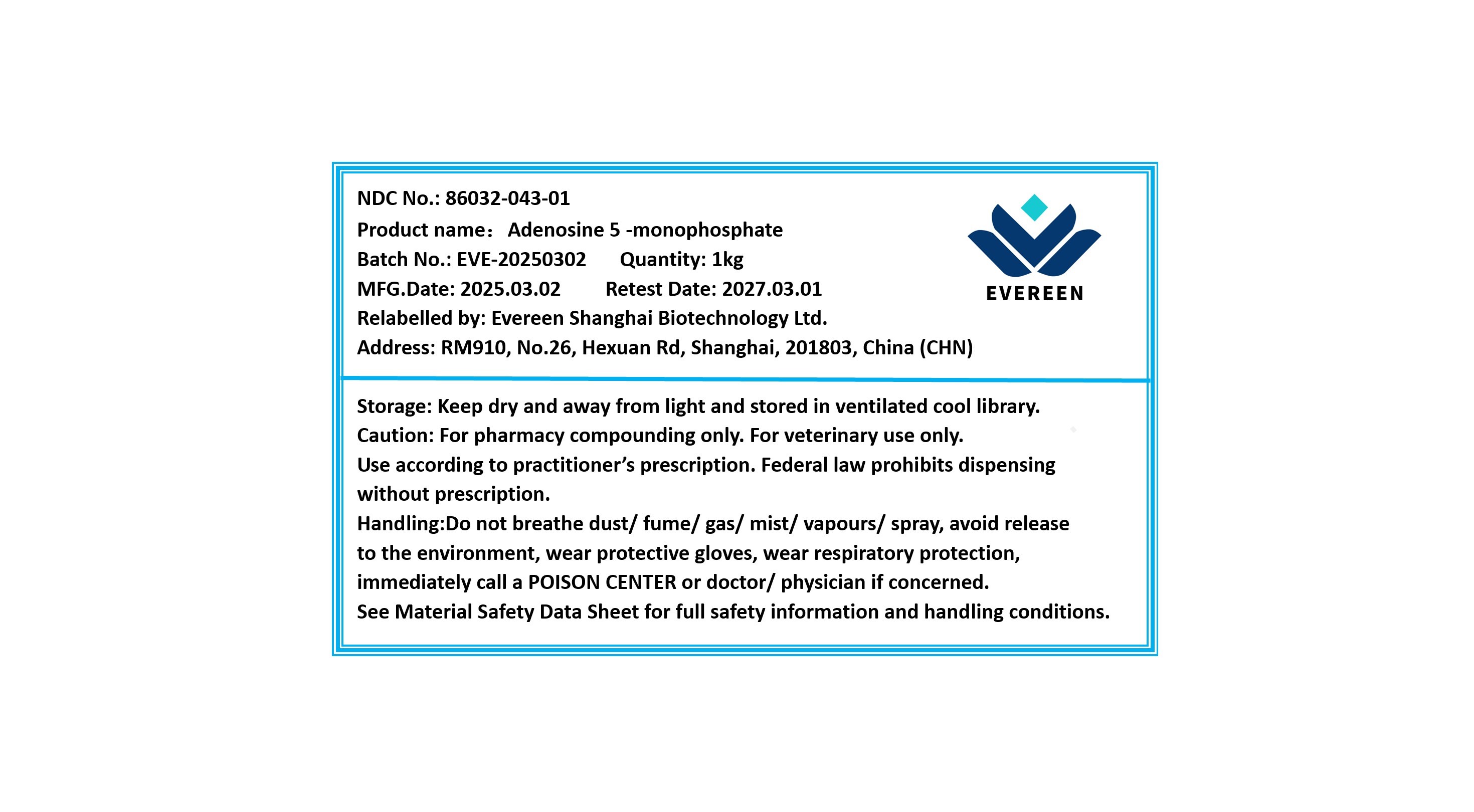 DRUG LABEL: Adenosine 5-monophosphate
NDC: 86032-043 | Form: POWDER
Manufacturer: Evereen Shanghai Biotechnology Ltd.
Category: other | Type: BULK INGREDIENT - ANIMAL DRUG
Date: 20250416

ACTIVE INGREDIENTS: ADENOSINE PHOSPHATE 1 kg/1 kg

Adenosine 5'-monophosphate